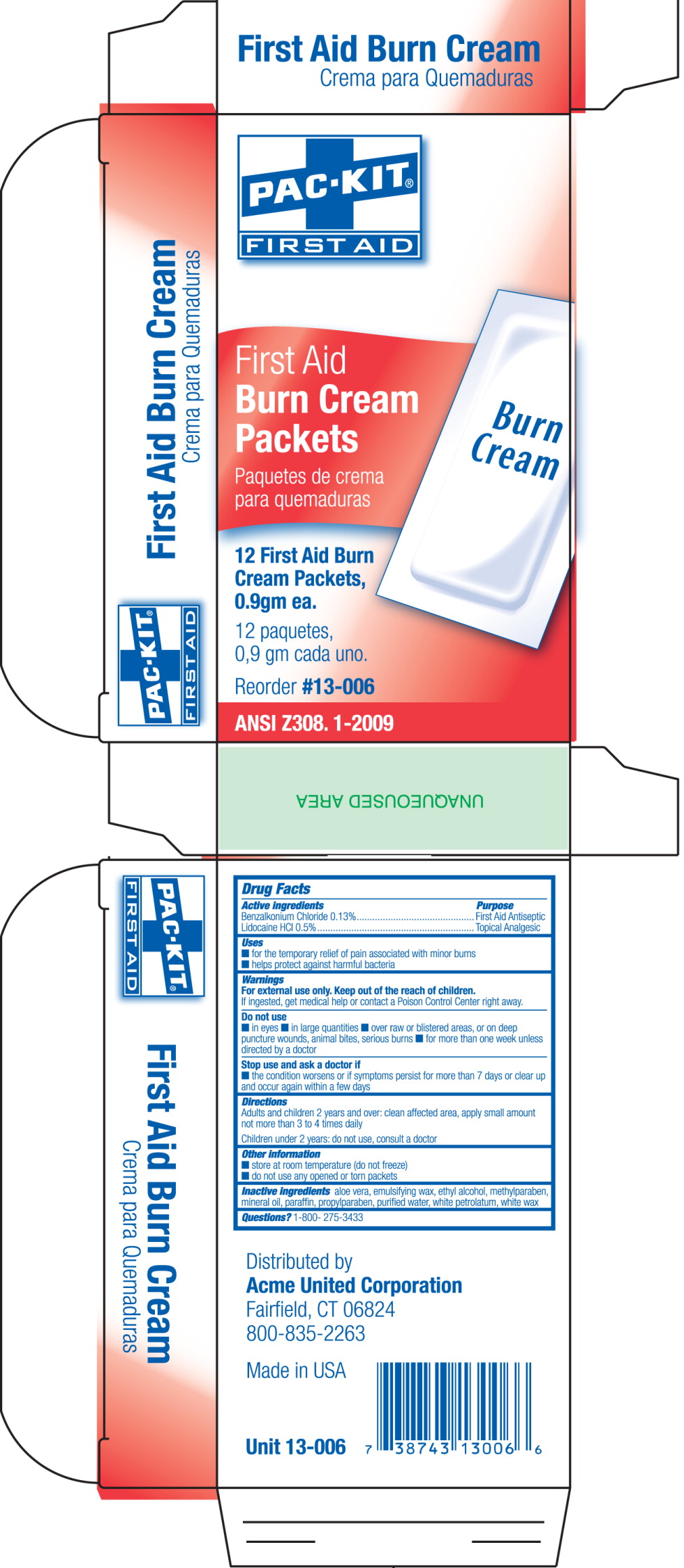 DRUG LABEL: First Aid and Burn
NDC: 0924-5701 | Form: CREAM
Manufacturer: Acme United Corporation
Category: otc | Type: HUMAN OTC DRUG LABEL
Date: 20120524

ACTIVE INGREDIENTS: benzalkonium chloride 1.3 mg/1 g; lidocaine hydrochloride 5 mg/1 g
INACTIVE INGREDIENTS: aloe vera leaf; alcohol; methylparaben; mineral oil; paraffin; propylparaben; water; petrolatum; white wax

Drug Facts

Active ingredients

Benzalkonium Chloride 0.13%

Lidocaine HCl 0.5%

Purpose

First Aid Antiseptic

Topical analgesic

Uses

- for the temporary relief of pain associated with minor burns
- helps protect against harmful bacteria

Warnings

For external use only

Keep out of reach of children.

If ingested, get medical help or contact a Poison Control Center right away.

Do not use

- in eyes
- in large quantities
- over raw or blistered areas, or on deep puncture wounds, animal bites, serious burns
- for more than one week unless directed by a doctor

Stop use and ask a doctor if

- the condition worsens or if symptoms persist for more than 7 days or clear up and occur again within a few days

Directions

Adults and children 2 years and over: clean affected area, apply small amount not more than 3 to 4 times daily

Children under 2 years: do not use, consult a doctor

Other information

- store at room temperature (do not freeze)
- do not use any opened or torn packets

Inactive ingredients

aloe vera, emulsifying wax, ethyl alcohol, methylparaben, mineral oil, paraffin, propylparaben, purified water, white petrolatum, white wax

Questions?

1-800-275-3433

PRINCIPAL DISPLAY PANEL – Pac-Kit 12 count box

PAC-KIT
FIRST AID

First Aid
Burn Cream
Packets

Paquetes de crema
para quemaduras

12 First Aid Burn
Cream Packets,
0.9gm ea.

12 paquetes,
0,9 gm cada uno.

Reorder #13-006

ANSI Z308. 1-2009